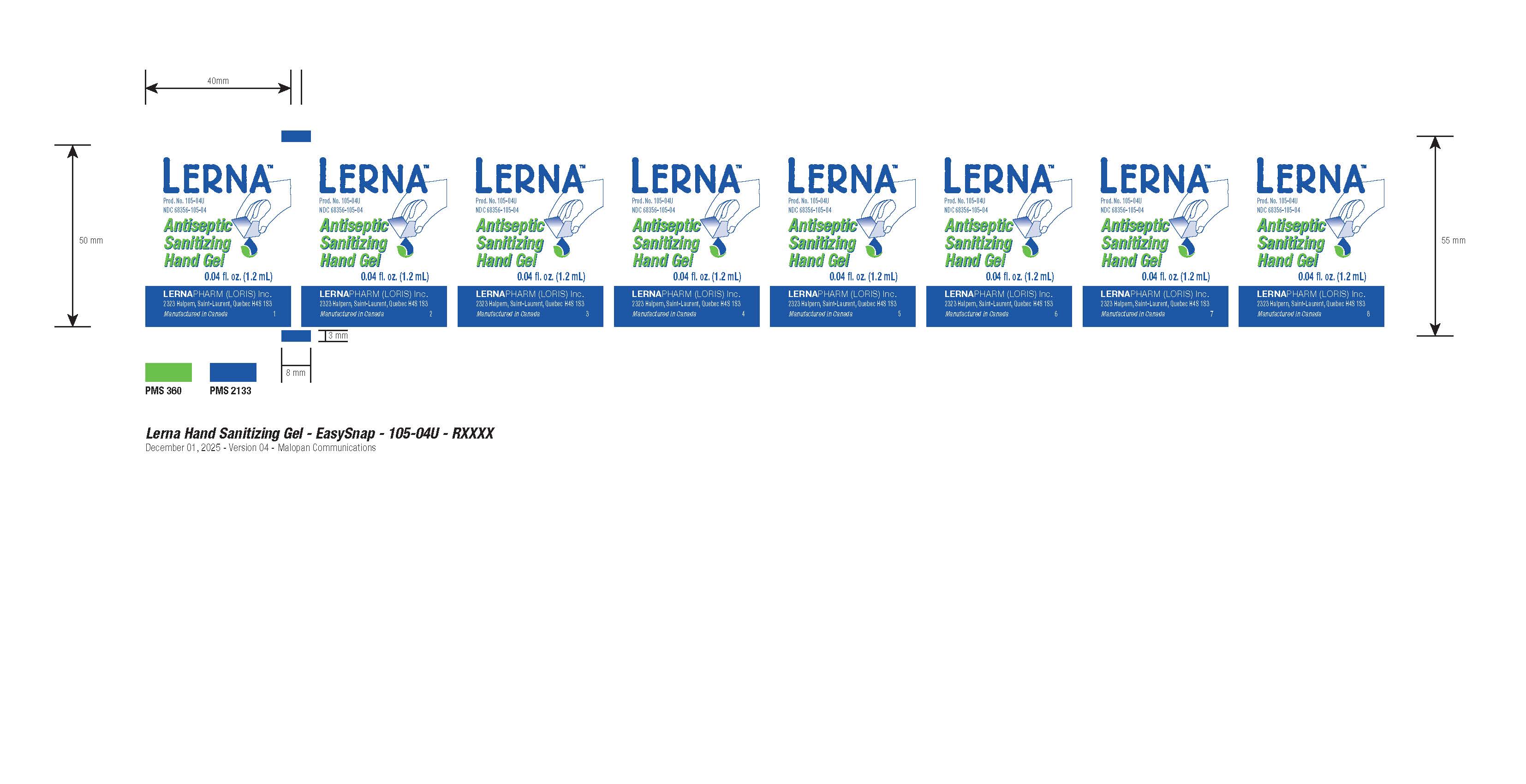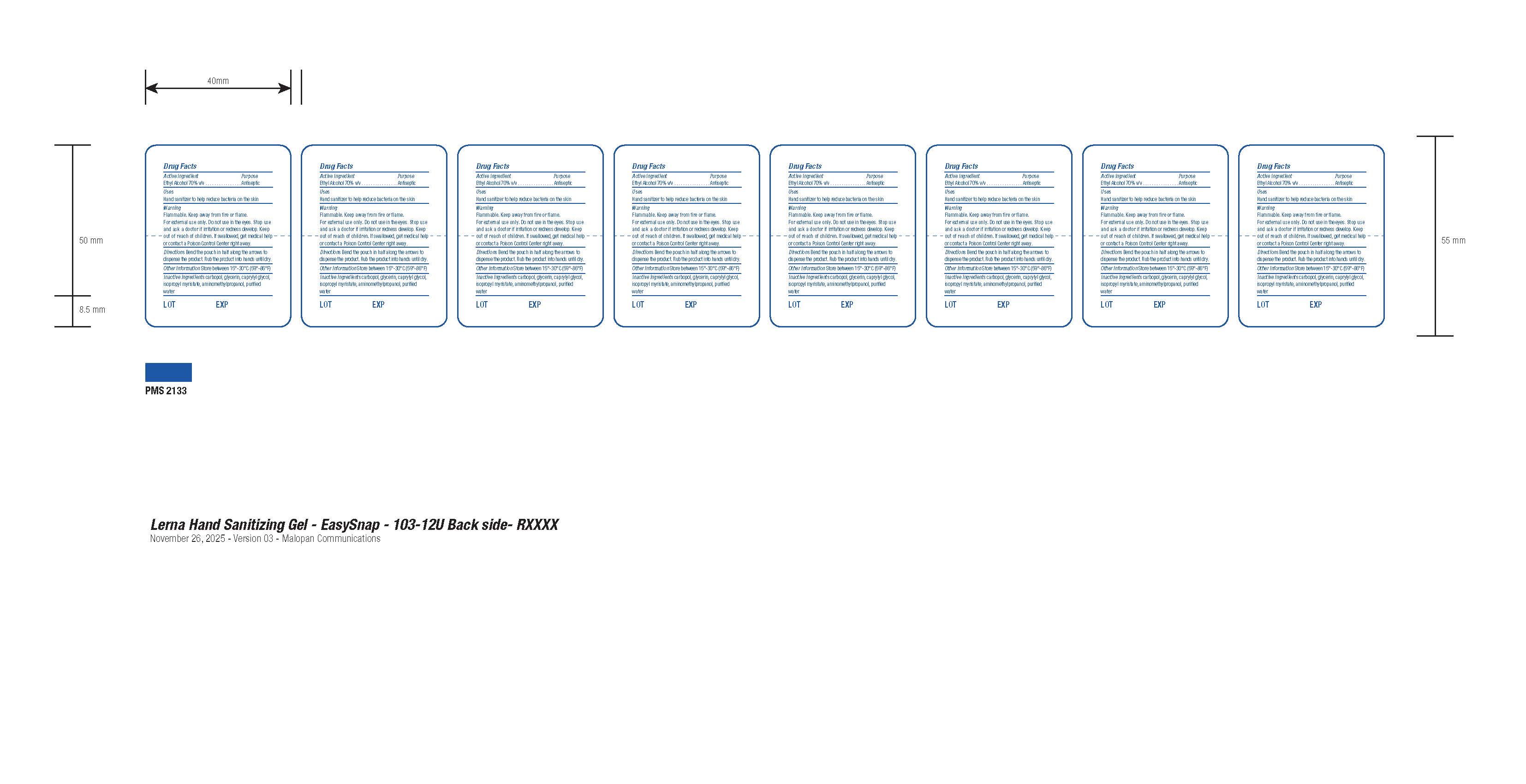 DRUG LABEL: Lerna Antiseptic Sanitizing Hand Gel
NDC: 68356-105 | Form: LIQUID
Manufacturer: Lernapharm Loris Inc.
Category: otc | Type: HUMAN OTC DRUG LABEL
Date: 20251123

ACTIVE INGREDIENTS: ALCOHOL 70 mL/100 mL
INACTIVE INGREDIENTS: WATER; AMINOMETHYLPROPANOL; GLYCERIN; CARBOMER; CAPRYLYL GLYCOL; ISOPROPYL MYRISTATE

Drug Facts - Lerna Antiseptic Sanitizing Hand Gel

Active Ingredient

Ethyl alcohol 70% v/v

Purpose

Antiseptic

Uses

Hand sanitizer to help reduce bacteria on skin

Warnings

Flammable. Keep away from fire or flame. For external use only. Do not use in the eyes.

Stop use and ask a doctor if

irritation or redness develop.

Keep out of reach of children.

If swallowed, get medical help or contact a Poison Control Center right away.

Directions

Bend the pouch in half along the arrows to dispense the product. Rub the product into hands until dry.

Other Information

Store between 15º-30ºC (59º-86ºF)

Inactive ingredients

carbopol, glycerin, caprylyl glycol, isopropyl myristate, aminomethylpropanol, purified water

Package Label - Principal Display Panel

NDC: 68356-105-04

Product: 105-04U

LERNA Antiseptic Sanitizing Hand Gel

0.04 fl. oz. (1.2 mL)

Lernapharm (Loris) Inc.

2323 Halpern, Saint-Laurent, Quebec H4S 1S3

Manufactured in Canada

LOT:

EXP.: